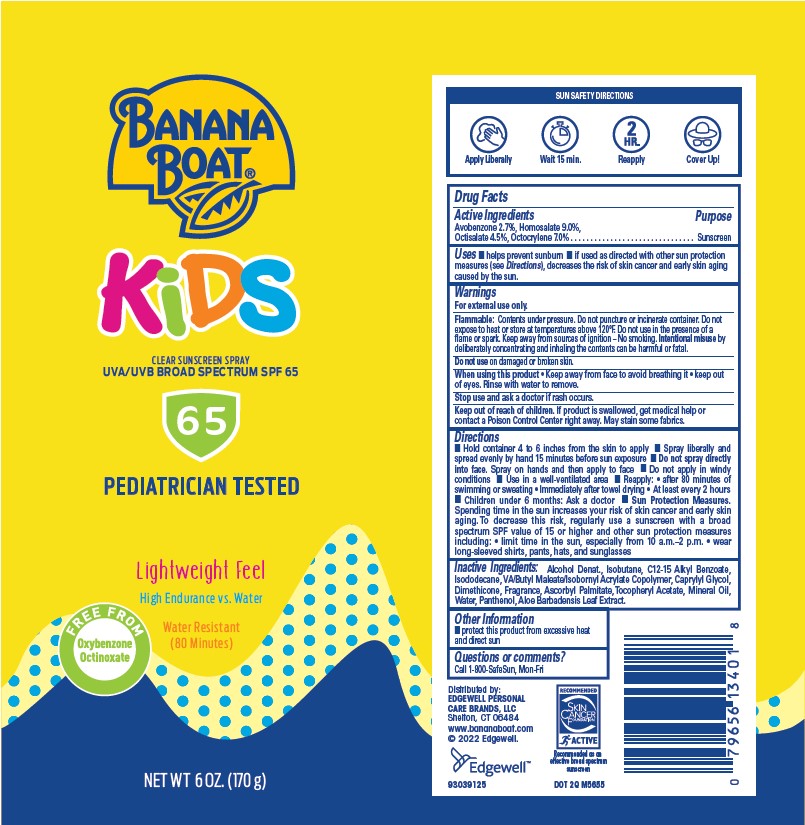 DRUG LABEL: BANANA BOAT KIDS SPF 65 CLEAR SUNSCREEN
NDC: 63354-821 | Form: AEROSOL, SPRAY
Manufacturer: Edgewell Personal Care Brands LLC
Category: otc | Type: HUMAN OTC DRUG LABEL
Date: 20241209

ACTIVE INGREDIENTS: OCTISALATE 4.5 g/100 g; AVOBENZONE 2.7 g/100 g; OCTOCRYLENE 7 g/100 g; HOMOSALATE 9 g/100 g
INACTIVE INGREDIENTS: DIMETHICONE; .ALPHA.-TOCOPHEROL ACETATE; PANTHENOL; ALKYL (C12-15) BENZOATE; CAPRYLYL GLYCOL; WATER; ASCORBYL PALMITATE; ISODODECANE; ALOE VERA LEAF; ALCOHOL; MINERAL OIL; ISOBUTANE

Active Ingredients

Avobenzone 2.7%, Homosalate 9.0%, Octisalate 4.5%, Octocrylene 7.0% . .

Purpose

Sunscreen

Uses

helps prevent sunburn • if used as directed with other sun protection measures (see Directions), decreases the risk of skin cancer and early skin aging caused by the sun.

Warnings

For external use only.

Flammable: Contents under pressure. Do not puncture or incinerate container. Do not expose to heat or store at temperatures above 120°F. Do not use in the presence of a flame or spark. Keep away from sources of ignition – No smoking. Intentional misuse by
deliberately concentrating and inhaling the contents can be harmful or fatal.

May stain some fabrics.

Do not use

on damaged or broken skin.

When using this product

• Keep away from face to avoid breathing it • keep out of eyes. Rinse with water to remove.

Stop use and ask a doctor

if rash occurs.

Keep out of reach of children.

If product is swallowed, get medical help or contact a Poison Control Center right away.

Directions

- Hold container 4 to 6 inches from the skin to apply
- Spray liberally and spread evenly by hand 15 minutes before sun exposure
- Do not spray directly into face. Spray on hands and then apply to face
- Do not apply in windy conditions
- Use in a well-ventilated area
- Reapply: • after 80 minutes ofswimming or sweating • Immediately after towel drying • At least every 2 hours
- Children under 6 months: Ask a doctor
- Sun Protection Measures. Spending time in the sun increases your risk of skin cancer and early skin aging. To decrease this risk, regularly use a sunscreen with a broad spectrum SPF value of 15 or higher and other sun protection measures including: • limit time in the sun, especially from 10 a.m.–2 p.m. • wear long-sleeved shirts, pants, hats, and sunglasses

Inactive Ingredients:

Alcohol Denat., Isobutane, C12-15 Alkyl Benzoate, Isododecane, VA/Butyl Maleate/Isobornyl Acrylate Copolymer, Caprylyl Glycol, Dimethicone, Fragrance, Ascorbyl Palmitate, Tocopheryl Acetate, Mineral Oil, Water, Panthenol, Aloe Barbadensis Leaf Extract.

Other Information

protect this product from excessive heat and direct sun

Questions or comments?

Call 1-800-SafeSun, Mon-Fri

PRINCIPAL DISPLAY PANEL

BANANA

BOAT

KiDS

CLEAR SUNSCREEN SPRAY

UVA/UVB BROAD SPECTRUM SPF 65

65

PEDIATRICIAN TESTED

Lightweight Feel

High Endurance vs. Water

Water Resistant

(80 Minutes)

NET WT 6 OZ. (170g)